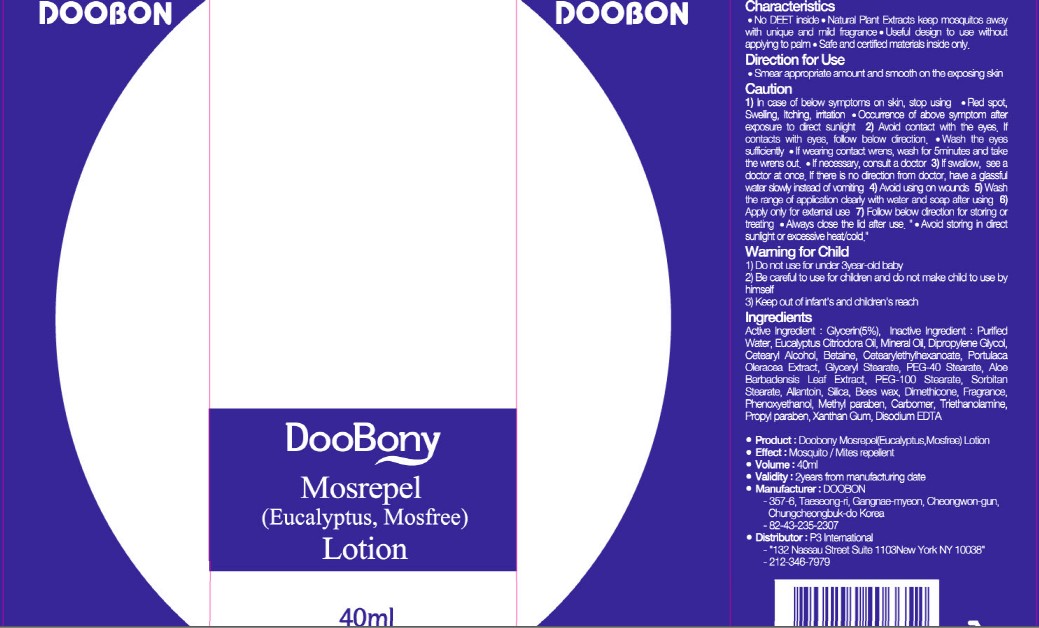 DRUG LABEL: DooBony Mosrepel
NDC: 50928-200 | Form: LOTION
Manufacturer: DOOBON INC
Category: otc | Type: HUMAN OTC DRUG LABEL
Date: 20100515

ACTIVE INGREDIENTS: GLYCERIN 2 mL/40 mL

DESCRIPTION

Characteristics:
- No DEET inside
- Natural Plan Extracts keep mosquitos away with unique and mild fragrance
- Useful design to use without applying to palm
- Safe and certified materials inside only

WHEN USING

Directions for Use
- Smear appropriate amount and smooth on the exposing skin

DO NOT USE

Cautionn
1) In case of below symptoms on skin, stop using
- Red spot, swelling, itching, irritation
- Occurrence of above symptom after exposure to direct sunlight
2) Avoid contact with the eyes. If contacts with eyes, follow below direction
- Wash the eyes sufficiently
- If wearing contact lenses, wash for 5 minutes and take the lenses out
- If necessary, consult a doctor
3) If swallowed, see a doctor at once. If there is no direction from doctor, take a glassful water slowly instead of vomiting
4) Avoid using on wounds
5) Wash the range of application clearly with water and soap after using
6) Apply only for external use
7) Follow below direction for storing or treating
- Always close the lid after use
- Avoid storing in direct sunlight or excessive heat/cold

KEEP OUT OF REACH OF CHILDREN

Warning for Child
1) Do not use for under 3 year-old baby
2) Be careful to use for children and do not make child to use by himself
3) Keep out of infant's and children's reach

Active Ingredient: Glycerin 5%

Inactive Ingredients:
Water, Eucalyptus Citriodora Oil, Mineral Oil, Dipropylene Glycol, Cetearyl Alcohol, Betaine, Cetearyl Ethylhexanoate, Portulaca Oleracea Extract, Glyceryl Stearate, PEG-40 Stearate, Aloe Barbadensis Leaf Extract, PEG-100 Stearate, Sorbitan Stearate, Allantoin, Silica, Bees wax, Dimethicone, Fragrance, Phenoxyethanol, Methylparaben, Carbomer, Triethanolamine, Propylparaben, Xanthan Gum, Disodium EDTA